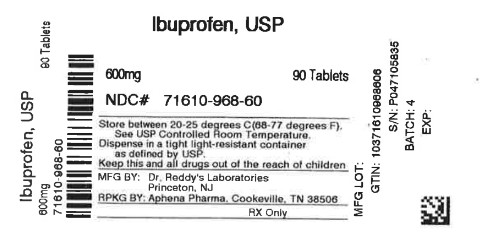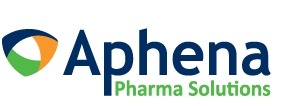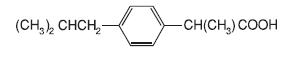 DRUG LABEL: Ibuprofen
NDC: 71610-968 | Form: TABLET
Manufacturer: Aphena Pharma Solutions - Tennessee, LLC		
Category: prescription | Type: HUMAN PRESCRIPTION DRUG LABEL
Date: 20260220

ACTIVE INGREDIENTS: IBUPROFEN 600 mg/1 1
INACTIVE INGREDIENTS: CARNAUBA WAX; SILICON DIOXIDE; CROSCARMELLOSE SODIUM; HYPROMELLOSES; MAGNESIUM STEARATE; CELLULOSE, MICROCRYSTALLINE; POLYDEXTROSE; POLYETHYLENE GLYCOL, UNSPECIFIED; POLYSORBATE 80; TITANIUM DIOXIDE

Ibuprofen Tablets

BOXED WARNING

Cardiovascular Thrombotic Events

- Nonsteroidal anti-inflammatory drugs (NSAIDs) cause an increased risk of serious cardiovascular thrombotic events, including myocardial infarction and stroke, which can be fatal. This risk may occur early in treatment and may increase with duration of use. (See WARNINGSand PRECAUTIONS).

- Ibuprofen tablets are contraindicated in the setting of coronary artery bypass graft (CABG) surgery (See CONTRAINDICATIONSand WARNINGS).

Gastrointestinal Risk

- NSAIDS cause an increased risk of serious gastrointestinaladverse events including bleeding, ulceration, and perforationof the stomach or intestines, which can be fatal. These eventscan occur at any time during use and without warning symptoms.Elderly patients are at greater risk for serious gastrointestinalevents. (See WARNINGS).

DESCRIPTION

Ibuprofen tablets contain the active ingredient ibuprofen, which is (±) -2 - (p- isobutylphenyl) propionic acid. Ibuprofen is a white powde rwith a melting point of 74-77° C and is very slightly soluble in water(<1 mg/mL) and readily soluble in organic solvents such as ethanol and acetone. The structural formula is represented below:

Ibuprofen, a nonsteroidal anti-inflammatory drug (NSAID), is availablein 400 mg, 600 mg, and 800 mg tablets for oral administration.Inactive ingredients: carnauba wax, colloidal silicon dioxide,croscarmellose sodium, hypromellose, magnesium stearate, microcrystallinecellulose, polydextrose, polyethylene glycol, polysorbate,titanium dioxide.

CLINICAL PHARMACOLOGY

Ibuprofen tablets contain ibuprofen which possesses analgesic andantipyretic activities. Its mode of action, like that of other NSAIDs, isnot completely understood, but may be related to prostaglandin synthetaseinhibition.

In clinical studies in patients with rheumatoid arthritis andosteoarthritis, Ibuprofen tablets have been shown to be comparableto aspirin in controlling pain and inflammation and to be associatedwith a statistically significant reduction in the milder gastrointestinalside effects (see ADVERSE REACTIONS). Ibuprofen may be well toleratedin some patients who have had gastrointestinal side effectswith aspirin, but these patients when treated with Ibuprofen tablets shouldbe carefully followed for signs and symptoms of gastrointestinalulceration and bleeding. Although it is not definitely known whether ibuprofen causes less peptic ulceration than aspirin, in one studyinvolving 885 patients with rheumatoid arthritis treated for up to oneyear, there were no reports of gastric ulceration with ibuprofen whereas frank ulceration was reported in 13 patients in the aspiringroup (statistically significant p<.001).

Gastroscopic studies at varying doses show an increased tendencytoward gastric irritation at higher doses. However, at comparabledoses, gastric irritation is approximately half that seen with aspirin.Studies using 51Cr-tagged red cells indicate that fecal blood lossassociated with Ibuprofen tablets in doses up to 2,400 mg daily didnot exceed the normal range, and was significantly less than thatseen in aspirin-treated patients.

In clinical studies in patients with rheumatoid arthritis, Ibuprofen has been shown to be comparable to indomethacin in controlling thesigns and symptoms of disease activity and to be associated with astatistically significant reduction of the milder gastrointestinal (see ADVERSE REACTIONS) and CNS side effects.

Ibuprofen may be used in combination with gold salts and/or corticosteroids.

Controlled studies have demonstrated that Ibuprofen is a more effective analgesic than propoxyphene for the relief of episiotomy pain, pain following dental extraction procedures, and for the relief ofthe symptoms of primary dysmenorrhea.

In patients with primary dysmenorrhea, Ibuprofen has been shown to reduce elevated levels of prostaglandin activity in the menstrualfluid and to reduce resting and active intrauterine pressure, as well asthe frequency of uterine contractions. The probable mechanism ofaction is to inhibit prostaglandin synthesis rather than simply to provide analgesia.

Pharmacodynamics

In a healthy volunteer study, ibuprofen 400 mg given once daily, administered 2 hours prior to immediate-release aspirin (81 mg) for 6 days, showed an interaction with the antiplatelet activity of aspirin as measured by % serum thromboxane B2 (TxB2) inhibition at 24 hours following the day-6 aspirin dose [53%]. An interaction was still observed, but minimized, when ibuprofen 400 mg given once-daily was administered as early as 8 hours prior to the immediate-release aspirin dose [90.7%]. However, there was no interaction with the antiplatelet activity of aspirin when ibuprofen 400 mg, given once daily, was administered 2 hours after (but not concomitantly, 15 min, or 30 min after) the immediate-release aspirin dose [99.2%].

In another study, where immediate-release aspirin 81 mg was administered once daily with ibuprofen 400 mg given three times daily (1, 7, and 13 hours post-aspirin dose) for 10 consecutive days, the mean % serum thromboxane B2 (TxB2) inhibition suggested no interaction with the antiplatelet activity of aspirin [98.3%]. However, there were individual subjects with serum TxB2 inhibition below 95%, with the lowest being 90.2%.

When a similarly designed study was conducted with enteric-coated aspirin, where healthy subjects were administered enteric-coated aspirin 81 mg once daily for 6 days and ibuprofen 400 mg three times daily (2, 7 and 12 h post-aspirin dose) for 6 days, there was an interaction with the antiplatelet activity at 24 hours following the day-6 aspirin dose [67%]. [See Precautions/Drug Interactions].

Pharmacokinetics

The ibuprofen in Ibuprofen tablets is rapidly absorbed. Peak serum ibuprofen levels are generally attained one to two hours after administration.With single doses up to 800 mg, a linear relationship exists between amount of drug administered and the integrated area underthe serum drug concentration vs time curve. Above 800 mg, however,the area under the curve increases less than proportional to increases in dose. There is no evidence of drug accumulation or enzyme induction.

The administration of Ibuprofen tablets either under fasting conditions or immediately before meals yields quite similar serum ibuprofen concentration-time profiles. When Ibuprofen is administered immediately after a meal, there is a reduction in the rate of absorption but no appreciable decrease in the extent of absorption.The bioavailability of the drug is minimally altered by the presence of food.

A bioavailability study has shown that there was no interference with the absorption of ibuprofen when given in conjunction with anantacid containing both aluminum hydroxide and magnesium hydroxide.

Ibuprofen is rapidly metabolized and eliminated in the urine. The excretion of ibuprofen is virtually complete 24 hours after the last dose. The serum half-life is 1.8 to 2 hours.

Studies have shown that following ingestion of the drug, 45% to79% of the dose was recovered in the urine within 24 hours as metabolite A (25%), (+)-2-[ p-(2hydroxymethyl-propyl) phenyl] propionic acid and metabolite B (37%), (+)-2-[ p-(2carboxypropyl)phenyl]propionic acid; the percentages of free and conjugated ibuprofen were approximately 1% and 14%, respectively.

INDICATIONS AND USAGE

Carefully consider the potential benefits and risks of Ibuprofentablets and other treatment options before deciding to use Ibuprofen.Use the lowest effective dose for the shortest duration consistent withindividual patient treatment goals (see WARNINGS).

Ibuprofen tablets are indicated for relief of the signs and symptoms of rheumatoid arthritis and osteoarthritis.

Ibuprofen tablets are indicated for relief of mild to moderate pain.

Ibuprofen tablets are also indicated for the treatment of primary dysmenorrhea.

Controlled clinical trials to establish the safety and effectiveness of Ibuprofen tablets in children have not been conducted.

CONTRAINDICATIONS

Ibuprofen tablets are contraindicated in patients with known hypersensitivityto ibuprofen.

Ibuprofen tablets should not be given to patients who have experienced asthma, urticaria, or allergic-type reactions after taking aspirin orother NSAIDs. Severe, rarely fatal, anaphylactic-like reactions to NSAIDs have been reported in such patients (see WARNINGS, Anaphylactoid Reactions, and PRECAUTIONS, Preexisting Asthma).

Ibuprofen tablets are contraindicated in the setting of coronary artery bypass graft (CABG) surgery(see WARNINGS).

WARNINGS

CARDIOVASCULAR EFFECTS

Cardiovascular Thrombotic Events

Clinical trials of several COX-2 selective and nonselective NSAIDs of up to three years duration have shown an increased risk of serious cardiovascular (CV) thrombotic events, including myocardial infarction (MI), and stroke, which can be fatal. Based on available data, it is unclear that the risk for CV thrombotic events is similar for all NSAIDs.The relative increase in serious CV thrombotic events over baseline conferred by NSAID use appears to be similar in those with and without known CV disease or risk factors for CV disease. However, patients with known CV disease or risk factors had a higher absolute incidence of excess serious CV thrombotic events, due to their increased baseline rate. Some observational studies found that this increased risk of serious CV thrombotic events began as early as the first weeks of treatment. The increase in CV thrombotic risk has been observed most consistently at higher doses.

To minimize the potential risk for an adverse CV event in NSAID-treated patients, use the lowest effective dose for the shortest duration possible. Physicians and patients should remain alert for the development of such events, throughout the entire treatment course, even in the absence of previous CV symptoms. Patients should be informed about the symptoms of serious CV events and the steps to take if they occur.

There is no consistent evidence that concurrent use of aspirin mitigates the increased risk of serious CV thrombotic events associated with NSAID use. The concurrent use of aspirin and an NSAID, such as ibuprofen, increases the risk of serious gastrointestinal (GI) events (see WARNINGS).

Status Post Coronary Bypass Graft (CABG) Surgery

Two large, controlled clinical trials of a COX-2 selective NSAID for the treatment of pain in the first 10 to 14 days following CABG surgery found an increased incidence of myocardial infarction and stroke. NSAIDs are contraindicated in the setting of CABG (see CONTRAINDICATIONS).

Post-MI Patients

Observational studies conducted in the Danish National Registry have demonstrated that patients treated with NSAIDs in the post-MI period were at increased risk of reinfarction, CV-related death, and all-cause mortality beginning in the first week of treatment. In this same cohort, the incidence of death in the first year post MI was 20 per 100 person years in NSAID-treated patients compared to 12 per 100 person years in non-NSAID exposed patients. Although the absolute rate of death declined somewhat after the first year post-MI, the increased relative risk of death in NSAID users persisted over at least the next four years to follow-up.

Avoid the use of Ibuprofen in patients with a recent MI unless the benefits are expected to outweigh the risk of recurrent CV thrombotic events. If Ibuprofen is used in patients with a recent MI, monitor patients for signs of cardiac ischemia.

Hypertension

NSAIDs including Ibuprofen tablets, can lead to onset of new hypertensionor worsening of preexisting hypertension, either of which maycontribute to the increased incidence of CV events. Patients takingthiazides or loop diuretics may have impaired response to these therapieswhen taking NSAIDs. NSAIDs, including Ibuprofen tablets, should beused with caution in patients with hypertension. Blood pressure (BP)should be monitored closely during the initiation of NSAID treatmentand throughout the course of therapy.

Heart Failure and Edema

The Coxib and traditional NSAID Trialists’ Collaboration meta-analysis of randomized controlled trails demonstrated an approximately two-fold increase in hospitalizations for heart failure in COX-2 selective-treated patients and nonselective NSAID-treated patients compared to placebo-treated patients. In a Danish National Registry study of patients with heart failure, NSAID use increased the risk of MI, hospitalization for heart failure, and death. Additionally, fluid retention and edema have been observed in some patients treated with NSAIDs. Use of ibuprofen may blunt the CV effects of several therapeutic agents used to treat these medical conditions [e.g., diuretics, ACE inhibitors, or angiotensin receptor blockers (ARBs)] [See DRUG INTERACTIONS]. Avoid the use of Ibuprofen tablets in patients with severe heart failure unless the benefits are expected to outweigh the risk of worsening heart failure. If Ibuprofen tablets is used in patients with severe heart failure, monitor patients for signs of worsening heart failure.

Gastrointestinal Effects - Risk of Ulceration, Bleeding, and Perforation

NSAIDs, including Ibuprofen tablets, can cause serious gastrointestinal(GI) adverse events including inflammation, bleeding, ulceration, and perforation of the stomach, small intestine, or large intestine, which can be fatal. These serious adverse events can occur at any time, with or without warning symptoms, in patients treated with NSAIDs. Only one in five patients, who develop a serious upper GI adverse event on NSAID therapy, is symptomatic. Upper GI ulcers, gross bleeding, or perforation caused by NSAIDs occur in approximately 1% of patientstreated for 3 to 6 months, and in about 2 to 4% of patients treated for oneyear. These trends continue with longer duration of use, increasing the likelihood of developing a serious GI event at some time during the course of therapy. However, even short-term therapy is not without risk. NSAIDs should be prescribed with extreme caution in thosewith a prior history of ulcer disease or gastrointestinal bleeding.Patients with a prior history of peptic ulcer disease and/or gastrointestinal bleeding who use NSAIDs have a greater than 10-fold increased risk for developing a GI bleed compared to patients treatedwith neither of these risk factors. Other factors that increase the riskof GI bleeding in patients treated with NSAIDs include concomitant use of oral corticosteroids or anticoagulants, longer duration of NSAID therapy, smoking, use of alcohol, older age, and poor general health status. Most spontaneous reports of fatal GI events are in elderly or debilitated patients and therefore, special care should be taken in treating this population. To minimize the potential risk for an adverse GI event in patients treated with an NSAID, the lowest effective dose should be used for the shortest possible duration. Patients and physicians should remain alert for signs and symptoms of GIulcerations and bleeding during NSAID therapy and promptly initiate additional evaluation and treatment if a serious GI event is suspected.This should include discontinuation of the NSAID until a serious GI adverse event is ruled out. For high-risk patients, alternate therapies that do not involve NSAIDs should be considered.

Renal Effects

Long-term administration of NSAIDs has resulted in renal papillary necrosis and other renal injury. Renal toxicity has also been seen in patients in whom renal prostaglandins have a compensatory role in the maintenance of renal perfusion. In these patients, administration of a NSAID may cause a dose dependent reduction in prostaglandin formation and, secondarily, in renal blood flow, which may precipitate overt renal decompensation. Patients at greatest riskof this reaction are those with impaired renal function, heart failure,liver dysfunction, those taking diuretics and ACE inhibitors, and the elderly. Discontinuation of NSAID therapy is usually followed by recovery to the pretreatment state.

Advanced Renal Disease

No information is available from controlled clinical studies regarding the use of Ibuprofen tablets in patients with advanced renal disease.Therefore, treatment with Ibuprofen tablets is not recommended in these patients with advanced renal disease. If Ibuprofen tablet therapy must be initiated, close monitoring of the patients renal function is advisable.

Anaphylactoid Reactions

As with other NSAIDs, anaphylactoid reactions may occur inpatients without known prior exposure to ibuprofen tablets. Ibuprofen tablets should not be given to patients with the aspirin triad. This symptom complex typically occurs in asthmatic patients who experience rhinitis with or without nasal polyps, or who exhibit severe, potentially fatal bronchospasm after taking aspirin or other NSAIDs (see CONTRAINDICATIONSand PRECAUTIONS, Preexisting Asthma).Emergency help should be sought in cases where an anaphylactoidreaction occurs.

Serious Skin Reactions

NSAIDs, including ibuprofen tablets, can cause serious skin adverse reactions such as exfoliative dermatitis, Stevens-Johnson Syndrome (SJS), and toxic epidermal necrolysis (TEN), which can be fatal. NSAIDs can also cause fixed drug eruption (FDE). FDE may present as a more severe variant known as generalized bullous fixed drug eruption (GBFDE), which can be life-threatening. These serious events may occur without warning. Inform patients about the signs and symptoms of serious skin reactions, and to discontinue the use of ibuprofen tablets at the first appearance of skin rash or any other sign of hypersensitivity. Ibuprofen tablets are contraindicated in patients with previous serious skin reactions to NSAIDs (see CONTRAINDICATIONS).

Drug Reaction with Eosinophilia and Systemic Symptoms (DRESS) has been reported in patients taking NSAIDs such as Ibuprofen. Some of these events have been fatal or life-threatening. DRESS typically, although not exclusively, presents with fever, reaction, lymphadenopathy, and/or facial swelling. Other clinical manifestations may include hepatitis, nephritis, hematological abnormalities, myocarditis, or myositis. Sometimes symptoms of DRESS may resemble an acute viral infection. Eosinophilia is often present. Because this disorder is variable in its presentation, other organ systems not noted here may be involved. It is important to note that early manifestations of hypersensitivity, such as fever or lymphadenopathy, may be present even though reaction is not evident. If such signs or symptoms are present, discontinue Ibuprofen and evaluate the patient immediately.

Pregnancy

Fetal Toxicity

Premature Closure of Fetal Ductus Arteriosus:

Avoid use of NSAIDs, including Ibuprofen, in pregnant women at about 30 week’s gestation and later. NSAIDs including Ibuprofen, increase the risk of premature closure of the fetal ductus arteriosus at approximately this gestational age.

Oligohydramnios/Neonatal Renal Impairment:

Use of NSAIDs, including Ibuprofen, at about 20 weeks gestation or later in pregnancy may cause fetal renal dysfunction leading to oligohydramnios and, in some cases, neonatal renal impairment. These adverse outcomes are seen, on average, after days to weeks of treatment, although oligohydramnios has been infrequently reported as soon as 48 hours after NSAID initiation.

Oligohydramnios is often, but not always, reversible with treatment discontinuation. Complications of prolonged oligohydramnios may, for example, include limb contractures and delayed lung maturation. In some postmarketing cases of impaired neonatal renal function, invasive procedures such as exchange transfusion or dialysis were required.

If NSAID treatment is necessary between about 20 weeks and 30 weeks gestation, limit Ibuprofen use to the lowest effective dose and shortest duration possible. Consider ultrasound monitoring of amniotic fluid if Ibuprofen treatment extends beyond 48 hours. Discontinue Ibuprofen if oligohydramnios occurs and follow up according to clinical practice [see PRECAUTIONS; Pregnancy]

PRECAUTIONS

General

Ibuprofen tablets cannot be expected to substitute for corticosteroids orto treat corticosteroid insufficiency. Abrupt discontinuation of corticosteroidsmay lead to disease exacerbation. Patients on prolongedcorticosteroid therapy should have their therapy tapered slowly if adecision is made to discontinue corticosteroids.

The pharmacological activity of Ibuprofen tablets in reducing fever andinflammation may diminish the utility of these diagnostic signs indetecting complications of presumed noninfectious, painful conditions.

Hepatic effects

Borderline elevations of one or more liver tests may occur in upto 15% of patients taking NSAIDs, including Ibuprofen tablets. These laboratoryabnormalities may progress, may remain unchanged, or maybe transient with continuing therapy. Notable elevations of ALT or AST (approximately three or more times the upper limit of normal)have been reported in approximately 1% of patients in clinical trialswith NSAIDs. In addition, rare cases of severe hepatic reactions,including jaundice, fulminant hepatitis, liver necrosis, and hepaticfailure, some of them with fatal outcomes have been reported. Apatient with symptoms and/or signs suggesting liver dysfunction, orwith abnormal liver test values, should be evaluated for evidence ofthe development of a more severe hepatic reaction while on therapy with Ibuprofen tablets. If clinical signs and symptoms consistent with liverdisease develop, or if systemic manifestations occur (e.g.,eosinophilia, reaction, etc.), Ibuprofen tablets should be discontinued.

Hematological effects

Anemia is sometimes seen in patients receiving NSAIDs, including Ibuprofen tablets. This may be due to fluid retention, occult or gross GIblood loss, or an incompletely described effect upon erythropoiesis.Patients on long-term treatment with NSAIDs, including Ibuprofen tablets,should have their hemoglobin or hematocrit checked if they exhibitany signs or symptoms of anemia.

In two postmarketing clinical studies the incidence of a decreasedhemoglobin level was greater than previously reported. Decrease inhemoglobin of 1 gram or more was observed in 17.1% of 193patients on 1,600 mg ibuprofen daily (osteoarthritis), and in 22.8% of189 patients taking 2,400 mg of ibuprofen daily (rheumatoid arthritis).Positive stool occult blood tests and elevated serum creatinine levelswere also observed in these studies.

NSAIDs inhibit platelet aggregation and have been shown to prolongbleeding time in some patients. Unlike aspirin, their effect onplatelet function is quantitatively less, of shorter duration, and reversible.

Patients receiving Ibuprofen tablets who may be adversely affected byalterations in platelet function, such as those with coagulation disordersor patients receiving anticoagulants should be carefully monitored.

Preexisting asthma

Patients with asthma may have aspirin-sensitive asthma. The useof aspirin in patients with aspirin-sensitive asthma has been associatedwith severe bronchospasm, which can be fatal. Since cross reactivity,including bronchospasm, between aspirin and NSAIDs hasbeen reported in such aspirin-sensitive patients, Ibuprofen tablets shouldnot be administered to patients with this form of aspirin sensitivityand should be used with caution in patients with preexisting asthma.

Ophthalmological effects.

Blurred and/or diminished vision, scotomata, and/or changes incolor vision have been reported. If a patient develops such complaintswhile receiving Ibuprofen tablets, the drug should be discontinued, and thepatient should have an ophthalmologic examination which includescentral visual fields and color vision testing.

Aseptic Meningitis

Aseptic meningitis with fever and coma has been observed on rareoccasions in patients on ibuprofen therapy. Although it is probablymore likely to occur in patients with systemic lupus erythematosusand related connective tissue diseases, it has been reported inpatients who do not have an underlying chronic disease. If signs orsymptoms of meningitis develop in a patient on Ibuprofen tablets, the possibilityof its being related to Ibuprofen tablets should be considered.

Information for Patients

Patients should be informed of the following information beforeinitiating therapy with an NSAID and periodically during the course ofongoing therapy. Patients should also be encouraged to read theNSAID Medication Guide that accompanies each prescription dispensed

• Cardiovascular Thrombotic Events: Advise patients to be alert for the symptoms of cardiovascular thrombotic events, including chest pain, shortness of breath, weakness, or slurring of speech, and to report any of these symptoms to their health care provider immediately [see WARNINGS].

• Ibuprofen tablets, like other NSAIDs, can cause GI discomfort and, rarely,serious GI side effects, such as ulcers and bleeding, which mayresult in hospitalization and even death. Although serious GI tractulcerations and bleeding can occur without warning symptoms,patients should be alert for the signs and symptoms of ulcerationsand bleeding, and should ask for medical advice when observingany indicative signs or symptoms including epigastric pain, dyspepsia,melena, and hematemesis. Patients should be apprised of theimportance of this follow-up (see WARNINGS, Gastrointestinal Effects-Risk of Ulceration, Bleeding and Perforation).

• Ibuprofen tablets, like other NSAIDs, can cause serious skin side effectssuch as exfoliative dermatitis, SJS and TEN, which may result inhospitalization and even death. Although serious skin reactions mayoccur without warning, patients should be alert for the signs andsymptoms of skin Reaction and blisters, fever, or other signs of hypersensitivitysuch as itching, and should ask for medical advice whenobserving any indicative sign or symptoms. Patients should beadvised to stop the drug immediately if they develop any type of eaction and contact their physicians as soon as possible.

• Serious Skin Reactions, including DRESS:Advise patients to stop taking ibuprofen tablets immediately if they develop any type of reaction or fever and to contact their healthcare provider as soon as possible [see WARNINGS].

• Heart Failure and Edema: Advise patients to be alert for the symptoms of congestive heart failure including shortness of breath, unexplained weight gain, or edema and to contact their healthcare provider if such symptoms occur [see WARNINGS].

• Patients should be informed of the warning signs and symptoms ofhepatotoxicity (e.g., nausea, fatigue, lethargy, pruritus, jaundice,right upper quadrant tenderness and “flu-like” symptoms). If theseoccur, patients should be instructed to stop therapy and seek immediatemedical therapy.

• Patients should be informed of the signs of an anaphylactoid reaction(e.g. difficulty breathing, swelling of the face or throat). If theseoccur, patients should be instructed to seek immediate emergencyhelp (see WARNINGS).

• In late pregnancy, as with other NSAIDs, Ibuprofen tablets should beavoided because it may cause premature closure of the ductus arteriosus.

Fetal Toxicity

Inform pregnant women to avoid use of Ibuprofen and other NSAIDs starting at 30 weeks gestation because of the risk of the premature closing of the fetal ductus arteriosus. If treatment with Ibuprofen is needed for a pregnant woman between about 20 to 30 weeks gestation, advise her that she may need to be monitored for oligohydramnios, if treatment continues for longer than 48 hours [see WARNINGS; Fetal Toxicity, PRECAUTIONS; Pregnancy].

Laboratory Tests

Because serious GI tract ulcerations and bleeding can occur withoutwarning symptoms, physicians should monitor for signs orsymptoms of GI bleeding. Patients on long-term treatment with NSAIDs should have their CBC and chemistry profile checked periodically.If clinical signs and symptoms consistent with liver or renaldisease develop, systemic manifestations occur (e.g., eosinophilia,reaction etc.), or abnormal liver tests persist or worsen, Ibuprofen tabletsshould be discontinued.

Drug Interactions

ACE-inhibitors:Reports suggest that NSAIDs may diminish the antihypertensiveeffect of ACE-inhibitors. This interaction should be given considerationin patients taking NSAIDs concomitantly with ACE-inhibitors.

Aspirin:

Pharmacodynamic studies have demonstrated interference with the antiplatelet activity of aspirin when ibuprofen 400 mg, given three times daily, is administered with enteric coated low-dose aspirin. The interaction exists even following a once-daily regimen of ibuprofen 400 mg, particularly when ibuprofen is dosed prior to aspirin. The interaction is alleviated if immediate-release low-dose aspirin is dosed at least 2 hours prior to a once daily regimen of ibuprofen; however, this finding cannot be extended to enteric-coated low-dose aspirin [see Clinical Pharmacology/Pharmacodynamics].

Because there may be an increased risk of cardiovascular events due to the interference of ibuprofen with the antiplatelet effect of aspirin, for patients taking low-dose aspirin for cardio protection who require analgesics, consider use of an NSAID that does not interfere with the antiplatelet effect of aspirin, or non-NSAID analgesics, where appropriate.

When Ibuprofen tablets are administered with aspirin, its protein bindingis reduced, although the clearance of free Ibuprofen tablets is notaltered. The clinical significance of this interaction is not known; however,as with other NSAIDs, concomitant administration of ibuprofenand aspirin is not generally recommended because of the potential forincreased adverse effects.

Diuretics

Clinical studies, as well as post marketing observations, haveshown that Ibuprofen tablets can reduce the natriuretic effect-offurosemide and thiazides in some patients. This response has beenattributed to inhibition of renal prostaglandin synthesis. During concomitanttherapy with NSAIDs, the patient should be observed closelyfor signs of renal failure (see PRECAUTIONS, Renal Effects), aswell as to assure diuretic efficacy.

Lithium

Ibuprofen produced an elevation of plasma lithium levels and areduction in renal lithium clearance in a study of eleven normal volunteers.The mean minimum lithium concentration increased 15%and the renal clearance of lithium was decreased by 19% during thisperiod of concomitant drug administration.This effect has been attributed to inhibition of renal prostaglandinsynthesis by ibuprofen. Thus, when ibuprofen and lithium are administeredconcurrently, subjects should be observed carefully for signsof lithium toxicity. (Read circulars for lithium preparation before useof such concurrent therapy.)

Methotrexate

NSAIDs have been reported to competitively inhibit methotrexateaccumulation in rabbit kidney slices. This may indicate that they couldenhance the toxicity of methotrexate. Caution should be used when NSAIDs are administered concomitantly with methotrexate.

Warfarin-type anticoagulants

Several short-term controlled studies failed to show that Ibuprofentablets significantly affected prothrombin times or a variety of otherclotting factors when administered to individuals on coumarin-typeanticoagulants. However, because bleeding has been reported when Ibuprofen tablets and other NSAIDs have been administered to patients oncoumarin-type anticoagulants, the physician should be cautiouswhen administering Ibuprofen tablets to patients on anticoagulants. Theeffects of warfarin and NSAIDs on GI bleeding are synergistic, suchthat the users of both drugs together have a risk of serious GI bleedinghigher than users of either drug alone.

H-2 Antagonists

In studies with human volunteers, co-administration of cimetidineor ranitidine with ibuprofen had no substantive effect on ibuprofenserum concentrations.

Pregnancy

Risk Summary

Use of NSAIDs, including Ibuprofen, can cause premature closure of the fetal ductus arteriosus and fetal renal dysfunction leading to oligohydramnios and, in some cases, neonatal renal impairment. Because of these risks, limit dose and duration of Ibuprofen use between about 20 and 30 weeks of gestation, and avoid Ibuprofen use at about 30 weeks of gestation and later in pregnancy [see WARNINGS; Fetal Toxicity].

Premature Closure of Fetal Ductus Arteriosus

Use of NSAIDs, including Ibuprofen, at about 30 weeks gestation or later in pregnancy increases the risk of premature closure of the fetal ductus arteriosus.

Oligohydramnios/Neonatal Renal Impairment

Use of NSAIDs at about 20 weeks gestation or later in pregnancy has been associated with cases of fetal renal dysfunction leading to oligohydramnios, and in some cases, neonatal renal impairment.

Data fromobservational studies regarding other potential embryofetal risks of NSAIDuse in women in the first or second trimesters of pregnancy areinconclusive. Reproductive studies conducted in rats and rabbits have notdemonstrated evidence of developmental abnormalities. However, animalreproduction studies are not always predictive of human response. Basedon animal data, prostaglandins have been shown to have an importantrole in endometrial vascular permeability, blastocyst implantation, anddecidualization. In animal studies, administration of prostaglandinsynthesis inhibitors such as ibuprofen, resulted in increased pre- and postimplantationloss. Prostaglandins also have been shown to have animportant role in fetal kidney development. In published animal studies,prostaglandin synthesis inhibitors have been reported to impair kidneydevelopment when administered at clinically relevant doses.

The estimated background risk of major birth defects and miscarriage for the indicated population(s) is unknown. All pregnancies have a background risk of birth defect, loss, or other adverse outcomes. In the U.S. general population, the estimated background risk of major birth defects and miscarriage in clinically recognized pregnancies is 2 to 4% and 15 to 20%, respectively.

Clinical Considerations

Fetal/Neonatal Adverse Reactions Premature Closure of Fetal Ductus Arteriosus:Avoid use of NSAIDs in women at about 30 weeks gestation and later in pregnancy, because NSAIDs, including Ibuprofen, can cause premature closure of the fetal ductus arteriosus (see WARNINGS; Fetal Toxicity).

Oligohydramnios/Neonatal Renal Impairment

If an NSAID is necessary at about 20 weeks gestation or later in pregnancy, limit the use to the lowest effective dose and shortest duration possible. If Ibuprofen treatment extends beyond 48 hours, consider monitoring with ultrasound for oligohydramnios. If oligohydramnios occurs, discontinue Ibuprofen and follow up according to clinical practice (see WARNINGS; Fetal Toxicity).

Data

Human Data

There are no adequate, well-controlled studies in pregnant women. Ibuprofen tablets should be used in pregnancy only if the potential benefit justifies the potential risk to the fetus.

Premature Closure of Fetal Ductus Arteriosus:

There are no adequate, well-controlled studies in pregnant women. Ibuprofen tablets should be used in pregnancy only if the potential benefit justifies the potential risk to the fetus.

Oligohydramnios/Neonatal Renal Impairment:

Published studies and postmarketing reports describe maternal NSAID use at about 20 weeks gestation or later in pregnancy associated with fetal renal dysfunction leading to oligohydramnios, and in some cases, neonatal renal impairment. These adverse outcomes are seen, on average, after days to weeks of treatment, although oligohydramnios has been infrequently reported as soon as 48 hours after NSAID initiation. In many cases, but not all, the decrease in amniotic fluid was transient and reversible with cessation of the drug. There have been a limited number of case reports of maternal NSAID use and neonatal renal dysfunction without oligohydramnios, some of which were irreversible. Some cases of neonatal renal dysfunction required treatment with invasive procedures, such as exchange transfusion or dialysis.

Methodological limitations of these postmarketing studies and reports include lack of a control group; limited information regarding dose, duration, and timing of drug exposure; and concomitant use of other medications. These limitations preclude establishing a reliable estimate of the risk of adverse fetal and neonatal outcomes with maternal NSAID use.

Because the published safety data on neonatal outcomes involved mostly preterm infants, the generalizability of certain reported risks to the full-term infant exposed to NSAIDs through maternal use is uncertain.

Labor and Delivery

In rat studies with NSAIDs, as with other drugs known to inhibitprostaglandin synthesis, an increased incidence of dystocia, delayedparturition, and decreased pup survival occurred. The effects of Ibuprofen tablets on labor and delivery in pregnant women are unknown.

Nursing Mothers

It is not known whether this drug is excreted in human milk.Because many drugs are excreted in human-milk and because of thepotential for serious adverse reactions in nursing infants from Ibuprofen tablets, a decision should be made whether to discontinue nursing ordiscontinue the drug, taking into account the importance of the drugto the mother.

Pediatric Use

Safety and effectiveness of Ibuprofen tablets in pediatric patients havenot been established.

Geriatric Use

As with any NSAIDs, caution should be exercised in treating theelderly (65 years and older).

ADVERSE REACTIONS

The most frequent type of adverse reaction occurring withIbuprofen tablets is gastrointestinal. In controlled clinical trials thepercentage of patients reporting one or more gastrointestinal complaintsranged from 4% to 16%.

In controlled studies when Ibuprofen tablets were compared toaspirin and indomethacin in equally effective doses, the overall incidenceof gastrointestinal complaints was about half that seen in eitherthe aspirin- or indomethacin-treated patients.

Adverse reactions observed during controlled clinical trials at anincidence greater than 1% are listed in the table. Those reactions listedin Column one encompass observations in approximately 3,000patients. More than 500 of these patients were treated for periods ofat least 54 weeks.

Still other reactions occurring less frequently than 1 in 100 werereported in controlled clinical trials and from marketing experience.These reactions have been divided into two categories: Column twoof the table lists reactions with therapy with Ibuprofen tablets wherethe probability of a causal relationship exists: for the reactions inColumn three, a causal relationship with Ibuprofen tablets has notbeen established.

Reported side effects were higher at doses of 3,200 mg/day thanat doses of 2,400 mg or less per day in clinical trials of patients withrheumatoid arthritis. The increases in incidence were slight and stillwithin the ranges reported in the table.

Incidence Greater than 1% (but less than 3%) Probable Causal Relationship* | Precise Incidence Unknown (but less than 1%) Probable Causal Relationship** | Precise Incidence Unknown (but less than 1%) Causal Relationship Unknown**
GASTROINTESTINALNausea*, epigastric pain*, heartburn*, diarrhea, abdominal distress, nausea and vomiting, indigestion, constipation, abdominal cramps or Pain, fullness of GI tract (bloating or flatulence). | Gastric or duodenal ulcer with bleeding and/or perforation, gastrointestinal hemorrhage, melena, gastritis, jaundice, abnormal liver function tests; pancreatitis
CENTRAL NERVOUS SYSTEMDizziness*, headache, nervousness | Depression, insomnia, confusion, emotional liability, somnolence, aseptic meningitis with fever and coma (see PRECAUTIONS) | Paresthesias, hallucinations, dream abnormalities, pseudotumor cerebri
DERMATOLOGICRash*, (including maculopapular type), pruritus | Vesiculobullous eruptions, urticaria, erythema multiforme, Stevens-Johnson syndrome, alopecia | Toxic epidermal necrolysis, photoallergic skin reactions
SPECIAL SENSESTinnitus | Hearing loss, amblyopia (blurred and/or diminished vision, sco-tomata and/or changes in color vision) (see PRECAUTIONS) | Conjunctivitis, diplopia, optic neuritis, cataracts
HEMATOLOGIC | Neutropenia, agranulocytosis, aplastic anemia, hemolytic anemia (sometimes Coombs positive), thrombocytopenia with or without purpura, eosinophilia, decreases in hemoglobin and hematocrit (see PRECAUTIONS) | Bleeding episodes (eg epistaxis, menorrhagia)
METABOLIC/ENDOCRINEDecreased appetite |  | Gynecomastia, hypoglycemic reaction, acidosis
CARDIOVASCULAREdema, fluid retention (generally responds promptly to drug discontinuation) (see PRECAUTIONS) | Congestive heart failure in patients with marginal cardiac function, elevate blood pressure, palpitations | Arrhythmias (sinus tachycardia, sinus bradycardia)
ALLERGIC | Syndrome of abdominal pain, fever, chills, nausea and vomiting; anaphylaxis; bronchospasm (see CONTRAINDICATIONS) | Serum sickness, lupus erythematosus syndrome. Henoch- Schonlein vasculitis, angiodema
RENAL | Acute renal failure (see PRECAUTIONS), decreased creatinine clearance, poliuria, azotemia, cystitis, Hematuria | Renal papillary necrosis
MISCELLANEOUS | Dry eyes and mouth, gingival ulcer, rhinitis

* Reactions occurring in 3% to 9% of patients treated with ibuprofen. (Those reactions occurring in less than 3% of the patients are unmarked.)

** Reactions are classified under “Probable Causal Relationship (PCR)” if there has been one positive rechallange or if three or more cases occur which might be causally related. Reactions are classified under “Causal Relationship Unknown” if seven or more events have been reported but the criteria for PCR have not been met.

Postmarketing Experience

The following adverse reactions have been identified during postapproval use of ibuprofen. Because these reactions are reported voluntarily from a population of uncertain size, it is not always possible to reliably estimate their frequency or establish a causal relationship to drug exposure.

Skin and Appendages: Exfoliative dermatitis, Stevens-Johnson Syndrome (SJS), toxic epidermal necrolysis (TEN), and fixed drug eruption (FDE).

OVERDOSAGE

Approximately 11⁄2hours after the reported ingestion of from 7 to10 Ibuprofen tablets (400 mg), a 19-month old child weighing 12 kgwas seen in the hospital emergency room, apneic and cyanotic,responding only to painful stimuli. This type of stimulus, however,was sufficient to induce respiration. Oxygen and parenteral fluidswere given; a greenish-yellow fluid was aspirated from the stomachwith no evidence to indicate the presence of ibuprofen. Two hoursafter ingestion the child’s condition seemed stable; she still respondedonly to painful stimuli and continued to have periods of apnea lastingfrom 5 to 10 seconds. She was admitted to intensive care andsodium bicarbonate was administered as well as infusions of dextroseand normal saline. By four hours post-ingestion she could bearoused easily, sit by herself and respond to spoken commands.Blood level of ibuprofen was 102.9 mcg/mL approximately 81⁄2hoursafter accidental ingestion. At 12 hours she appeared to be completelyrecovered.

In two other reported cases where children (each weighingapproximately 10 kg) accidentally, acutely ingested approximately120 mg/kg, there were no signs of acute intoxication or late sequelae.Blood level in one child 90 minutes after ingestion was 700 mcg/mL —about 10 times the peak levels seen in absorption-excretion studies.A 19-year old male who had taken 8,000 mg of ibuprofen over aperiod of a few hours complained of dizziness, and nystagmus wasnoted. After hospitalization, parenteral hydration and three days bedrest, he recovered with no reported sequelae.

In cases of acute overdosage, the stomach should be emptied byvomiting or lavage, though little drug will likely be recovered if morethan an hour has elapsed since ingestion. Because the drug is acidicand is excreted in the urine, it is theoretically beneficial to administeralkali and induce diuresis. In addition to supportive measures, the useof oral activated charcoal may help to reduce the absorption andreabsorption of Ibuprofen tablets.

DOSAGE AND ADMINISTRATION

Carefully consider the potential benefits and risks of Ibuprofen tabletsand other treatment options before deciding to use Ibuprofen tablets. Usethe lowest effective dose for the shortest duration consistent withindividual patient treatment goals (see WARNINGS).

After observing the response to initial therapy with Ibuprofen tablets, thedose and frequency should be adjusted to suit an individual patient’sneeds.Do not exceed 3200 mg total daily dose. If gastrointestinal complaintsoccur, administer Ibuprofen tablets with meals or milk.

Rheumatoid arthritis and osteoarthritis, including flare-ups ofchronic disease:

Suggested Dosage: 1,200 mg to 3,200 mg daily (400 mg, 600 mg or 800 mg tid or qid). Individual patients may show a better responseto 3200 mg daily, as compared with 2,400 mg, although in well-controlledclinical trials patients on 3,200 mg did not show a better meanresponse in terms of efficacy. Therefore, when treating patients with 3,200 mg/day, the physician should observe sufficient increased clinicalbenefits to offset potential increased risk.The dose should be tailored to each patient, and may be loweredor raised depending on the severity of symptoms either at time of initiatingdrug therapy or as the patient responds or fails to respond.In general, patients with rheumatoid arthritis seem to require higherdoses of Ibuprofen tablets than do patients with osteoarthritis.

The smallest dose of Ibuprofen tablets that yields acceptable controlshould be employed. A linear blood level dose-response relationshipexists with single doses up to 800 mg (See CLINICAL PHARMACOLOGYfor effects of food on rate of absorption).

The availability of three tablet strengths facilitates dosage adjustment.In chronic conditions, a therapeutic response to therapy with Ibuprofen tablets is sometimes seen in a few days to a week but most often isobserved by two weeks. After a satisfactory response has beenachieved, the patient’s dose should be reviewed and adjusted asrequired.

Mild to moderate pain:

400 mg every 4 to 6 hours as necessaryfor relief of pain.In controlled analgesic clinical trials, doses of Ibuprofen tabletsgreater than 400 mg were no more effective than the 400 mg dose.

Dysmenorrhea:

For the treatment of dysmenorrhea, beginningwith the earliest onset of such pain, Ibuprofen tablets should be given in adose of 400 mg every 4 hours as necessary for the relief of pain.

HOW SUPPLIED

Ibuprofen tablets are available in the following strengths, colors and sizes:

400 mg : Oval shaped, white, film-coated tablet debossed "4I" on one side.

Bottles of 100 NDC 51407-839-01

Bottles of 500 NDC 51407-839-05

600 mg : Caplet shaped, white, film-coated tablet Debossed "6I" on one side.

Bottles of 100 NDC 51407-840-01

Bottles of 500 NDC 51407-840-05

800 mg : Caplet shaped, white, film-coated tablet debossed "8I" on one side.

Bottles of 100 NDC 51407-841-01

Bottles of 500 NDC 51407-841-05

Store at room temperature. Avoid excessive heat 40°C (104°F).

Revised: 09/2025

Marketed by:
GSMS, Inc.
Camarillo, CA 93012 USA

MEDICATION GUIDE

Medication Guide for Non-Steroidal Anti-Inflammatory Drugs (NSAIDs)

What is the most important information I should know about medicines called Non-Steroidal Anti-Inflammatory Drugs (NSAIDs)?

NSAIDs can cause serious side effects, including:

• Increased risk of a heart attack or stroke that can lead to death.This risk may happen early in treatment and may increase:

° with increasing doses of NSAIDs

° with longer use of NSAIDs

Do not take NSAIDs right before or after a heart surgery called a "coronary artery bypass graft (CABG)."

Avoid taking NSAIDs after a recent heart attack, unless your healthcare provider tells you to. You may have an increased risk of another heart attack if you take NSAIDs after a recent heart attack.

•Increased risk of bleeding, ulcers, and tears (perforation) of the esophagus (tube leading from the mouth to the stomach), stomach and intestines:

° anytime during use

° without warning symptoms

° that may cause death

The risk ofgetting an ulcer or bleeding increases with:

° past history of stomach ulcers, or stomach or intestinal bleeding with use of NSAIDs

° taking medicines called "corticosteroids", "anticoagulants", "SSRIs", or "SNRIs"

° increasing use of NSAIDs

° longer use of NSAIDs

° smoking

° drinking alcohol

° older age

° poor health

° advanced liver disease

° bleeding problems

NSAIDs should only be used:

° exactly as prescribed

° at the lowest dose possible for your treatment

° for the shortest time needed

What are NSAIDs?

NSAIDs are used to treat pain and redness, swelling, and heat (inflammation) from medical conditions such as different types of arthritis, menstrual cramps, and other types of short-term pain.

Who should not NSAIDs?

Do not take NSAIDs:

• if you had an asthma attack, hives, or other allergic reaction with aspirin or any other NSAIDs

• right before or after heart bypass surgery

Before taking NSAIDs, tell your healthcare provider about all your medical conditions, including if you:

• have liver or kidney problems

• have high blood pressure

• have asthma

• are pregnant or plan to become pregnant. Taking NSAIDs at about 20 weeks of pregnancy or later may harm your unborn baby. If you need to take NSAIDs for more than 2 days when you are between 20 and 30 weeks of pregnancy, your healthcare provider may need to monitor the amount of fluid in your womb around your baby. You should not take NSAIDs after about 30 weeks of pregnancy.

• are breastfeeding or plan to breast feed

Tell your healthcare provider about all of the medicines you take, including prescription or over-the-counter medicines, vitamins or herbal supplements.NSAIDs and some other medicines can interact with each other and cause serious side effects. Do not start taking any new medicine without talking to your healthcare provider first.

What are the possible side effects of NSAIDs?

NSAIDs can cause serious side effects, including:

See "What is the most important information I should know about medicines called Nonsterodial Anti-Inflammatory Drugs (NSAIDs)?"

• new or worse high blood pressure • low red blood cells (anemia)

• heart failure • life-threatening skin reactions

• liver problems including liver failure • life-threatening allergic reactions

• kidney problems including kidney failure

• Other side effects of NSAIDs include:stomach pain, constipation, diarrhea, gas, heartburn, nausea, vomiting, and dizziness.

Get emergency help right away if you have any of the following symptoms:

• shortness of breath or trouble breathing • slurred speech

• chest pain • swelling of the face or throat

• weakness in one part or side of your body

Stop your NSAID medicine and call your healthcare provider right away if you have any of thefollowing symptoms:

• nausea • vomit blood

• more tired or weaker than usual • there is blood in your bowel movement or it is black and sticky like tar

• diarrhea • unusual weight gain

• itching • skin reaction or blisters with fever

• your skin or eyes look yellow • swelling of the arms, legs, hands and feet

• indigestion or stomach pain • flu-like symptoms

If you take too much of your NSAIDs, call your healthcare provider or get medical help right away.

These are not all the possible side effects of NSAIDs. For more information, ask your healthcare provider or pharmacist about NSAIDs.

Call your doctor for medical advice about side effects. You may report side effects to FDA at 1-800-FDA-1088.

Other information about NSAIDs

•Aspirin is an NSAID but it does not increase the chance of a heart attack. Aspirin can cause bleeding in the brain, stomach, and intestines. Aspirin can also cause ulcers in the stomach and intestines.

• Some of NSAIDs are sold in lower doses without a prescription (over-the-counter) Talk to your healthcare provider before using over- the-counter NSAIDs for more than 10 days.

General information about the safe and effective use of NSAIDs

Medicines are sometimes prescribed for purposes other than those listed in a Medication Guide. Do not us NSAIDs for a condition for which it was not prescribed. Do not give NSAIDs to other people, even if they have the same symptoms that you have. It may harm them.

If you would like more information about NSAIDs, talk with your healthcare provider. You can ask your pharmacist or healthcare provider for information about NSAIDs that is written for professionals

This Medication Guide has been approved by the U.S. Food and Drug Administration

Revised: 09/2025

Print Medication Guide at: https://gsms.us/

Marketed by:
GSMS, Inc.
Camarillo, CA 93012 USA

REPACKAGING INFORMATION

Please reference the HOW SUPPLIED section listed above for a description of individual drug products listed below. This drug product has been received by Aphena Pharma Solutions - Tennessee, LLC in a manufacturer or distributor packaged configuration and repackaged in full compliance with all applicable cGMP regulations. The package configurations available from Aphena are listed below:

600mg
NDC 71610-968-53, Bottles of 60 Tablets
NDC 71610-968-60, Bottles of 90 Tablets
NDC 71610-968-80, Bottles of 180 Tablets
NDC 71610-968-92, Bottles of 270 Tablets

Store between 20°-25°C (68°-77°F). See USP Controlled Room Temperature. Dispense in a tight light-resistant container as defined by USP. Keep this and all drugs out of the reach of children.
Repackaged by:
Cookeville, TN 38506
20260220BSC

PRINCIPAL DISPLAY PANEL - 600mg

NDC 71610-968 - Ibuprofen, USP 600mg Tablets - Rx Only